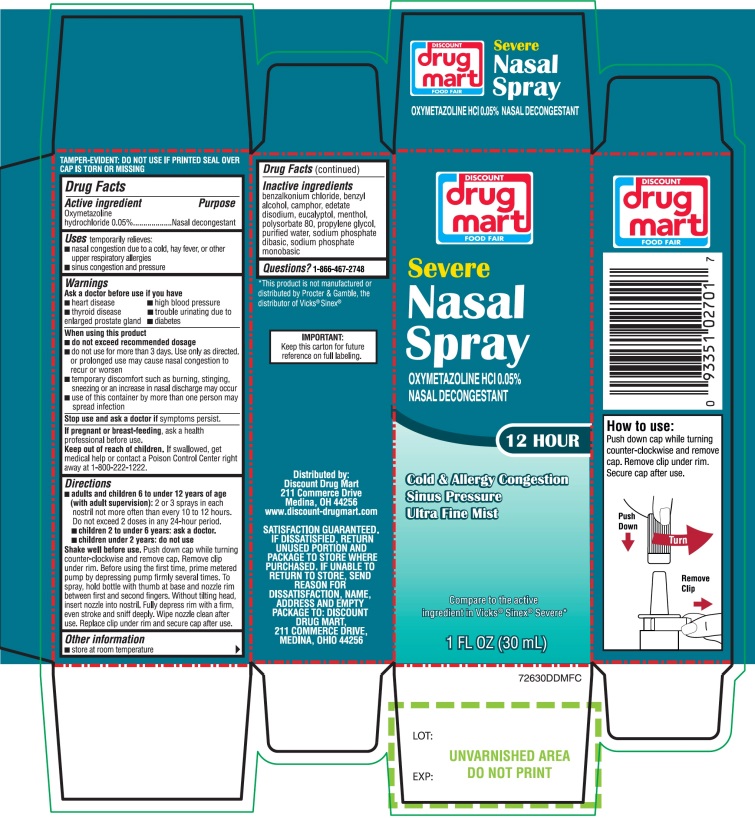 DRUG LABEL: Discount Drug Mart

NDC: 53943-726 | Form: SPRAY
Manufacturer: DISCOUNT DRUG MART
Category: otc | Type: HUMAN OTC DRUG LABEL
Date: 20250911

ACTIVE INGREDIENTS: OXYMETAZOLINE HYDROCHLORIDE 0.05 g/100 mL
INACTIVE INGREDIENTS: BENZALKONIUM CHLORIDE; BENZYL ALCOHOL; EDETATE DISODIUM; EUCALYPTOL; MENTHOL, UNSPECIFIED FORM; POLYSORBATE 80; PROPYLENE GLYCOL; WATER; SODIUM PHOSPHATE, DIBASIC, UNSPECIFIED FORM; SODIUM PHOSPHATE, MONOBASIC, UNSPECIFIED FORM

Drug Mart Severe Nasal Spray Drug Facts

Active ingredient

Oxymetazoline hydrochloride 0.05%

Purpose

Nasal Decongestant

Uses

temporarily relieves

- nasal congestion due to a cold, heavy fever, or other upper respiratory allergies
- Sinus congestion and pressure

Ask a doctor before use if you have

- heart disease
- high blood pressure
- diabetes
- thyroid disease
- trouble urinating due to an enlarged prostate gland

When using this product

- do not exceed recommended dosage
- do not use this product for more than 3 days. Use only as directed. Frequent or prolonged use may cause nasal congestion to recur or worsen.
- temporary discomfort such as burning, stinging, sneezing or an increase in nasal discharge may occur
- use of this container by more than one person may spread infection

Stop use and ask a doctor if

- symptoms persist

If pregnant or breast-feeding,

ask a health professional before use.

Keep out of reach of children.

If swallowed, get medical help or contact a Poison Control Center right away at (1-800-222-1222).

Directions

- adults & children 6 to under 12 years of age & older (with adult supervision):2 or 3 sprays in each nostril not more often than every 10 to 12 hours. Do not exceed 2 doses in any 24-hour period.
- children 2 to under 6 years:ask a doctor
- children 2 years:do not use

Shake well before use.Push down cap while turning counter-clockwise and remove cap .Remove clip under rim. Before using the first time, prime metered pump by depressing pump firmly several times. To spray, hold bottle with thumb at base and nozzle between first and second fingers. Without titling head, insert nozzle into nostril. Fully depress rim with a firm, even stroke and sniff deeply. Wipe nozzle clean after use. Replace clip under rim and secure cap after use.

Other information

- store at room temperature

Inactive ingredients

benzalkonium chloride, benzyl alcohol, edetate disodium, eucalyptol, menthol, polysorbate 80, propylene glycol, purified water, sodium phosphate dibasic, sodium phosphate monobasic.

Questions or comments?

1-866-467-2748

Principal Display Panel

DISCOUNT drug mart

FOOD FAIR

NDC# 53943-726-30

Compare to the active ingredient in Vicks® Sinex® Severe*

Severe Nasal Spray

OXYMETAZOLINE HCl 0.05%

NASAL DECONGESTANT

12 HOUR

Cold & allergy congestion

Sinus pressure

Ultra-Fine Mist

1 FL OZ (30 mL)

IMPORTANT:Keep the carton for future reference on full labeling

Distributed by:

Discount Drug Mart

211 Commerce Drive

Medina, OH 44256

www.discount-drugmart.com

SATISFACTION GUARANTEED. IF DISSATISFIED, RETURN UNUSED PORTION AND PACKAGE TO STORE WHERE PURCHASED. IF UNABLE TO RETURN TO STORE, SEND REASON FOR DISSATISFACTION, NAME, ADDRESS AND EMPTY PACKAGE TO: DISCOUNT DRUG MART, 211 COMMERCE DRIVE MEDINA, OHIO 44256.

*This product is not manufactured or distributed by Procter and Gamble, the distributer of Vicks®Sinex®